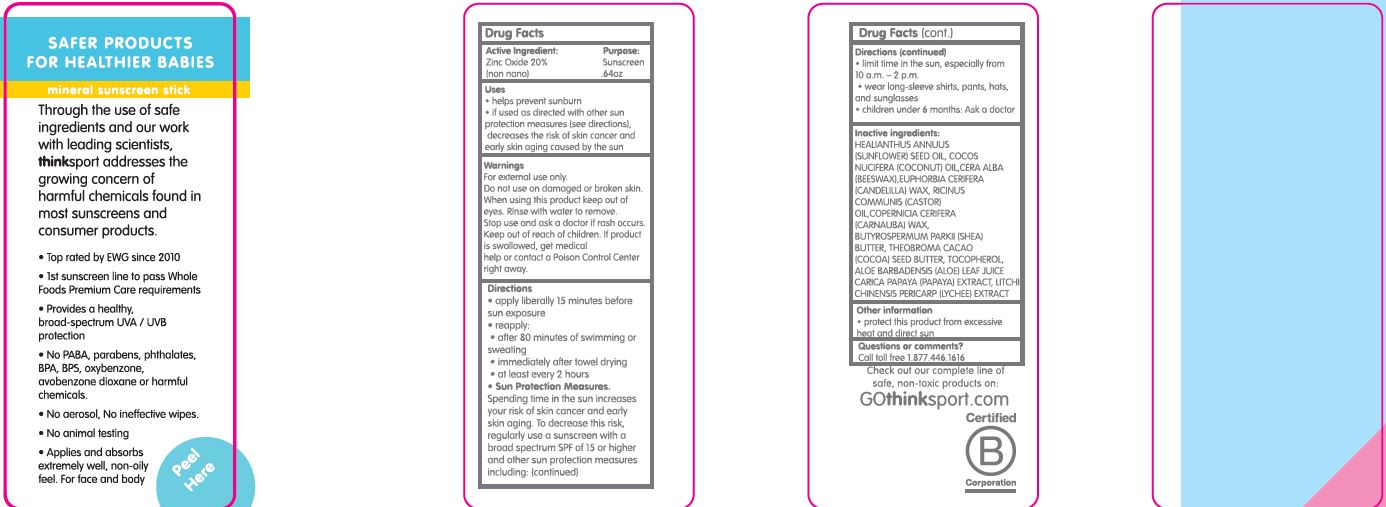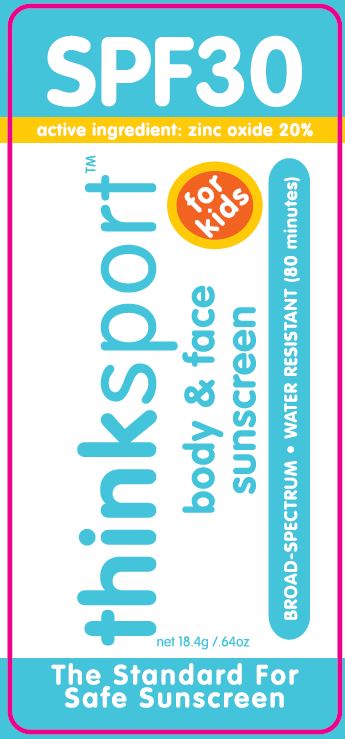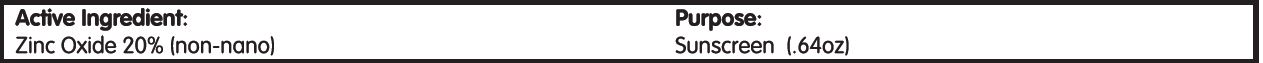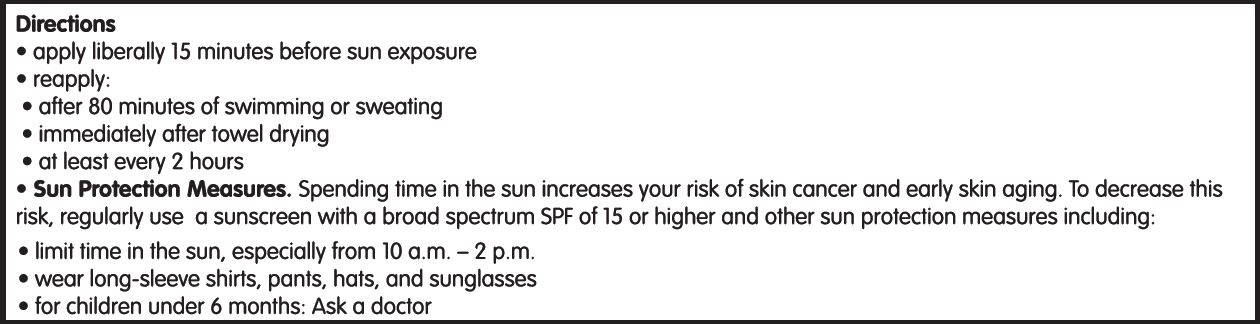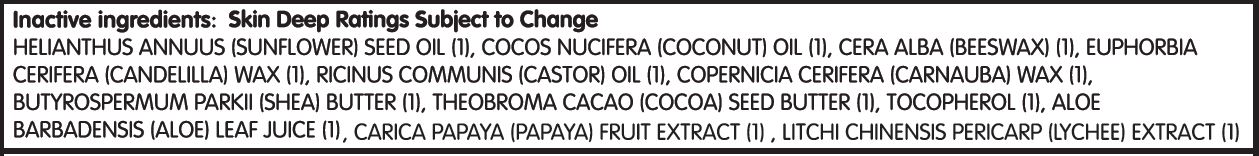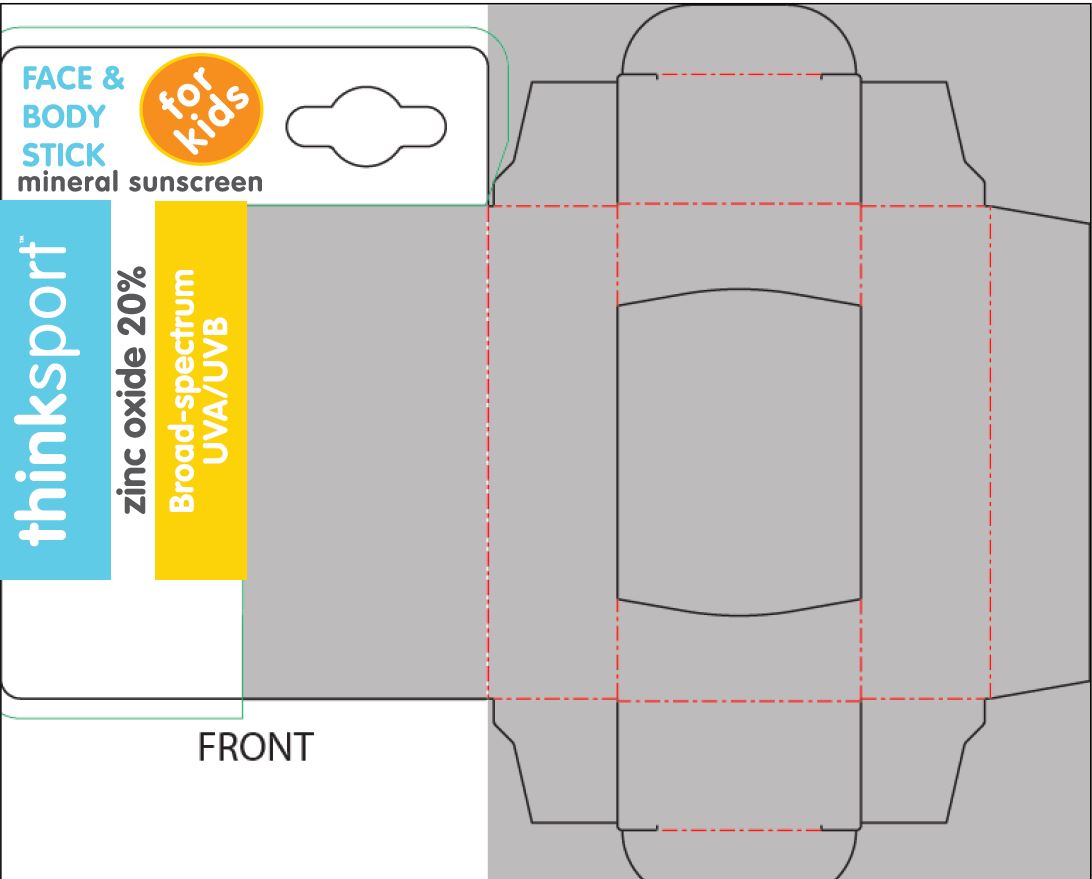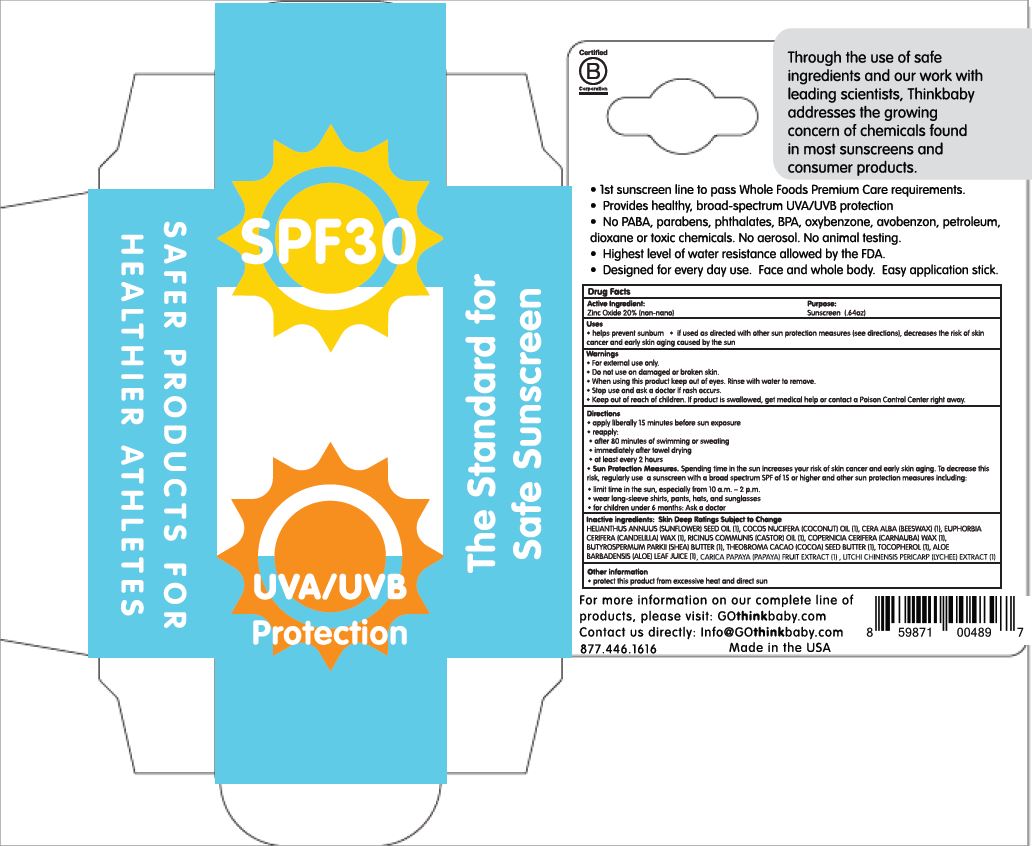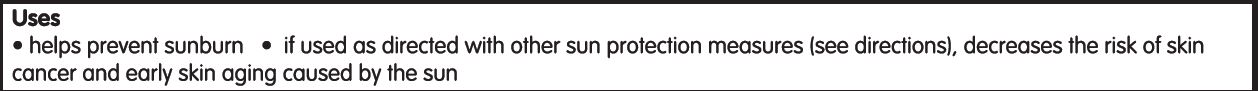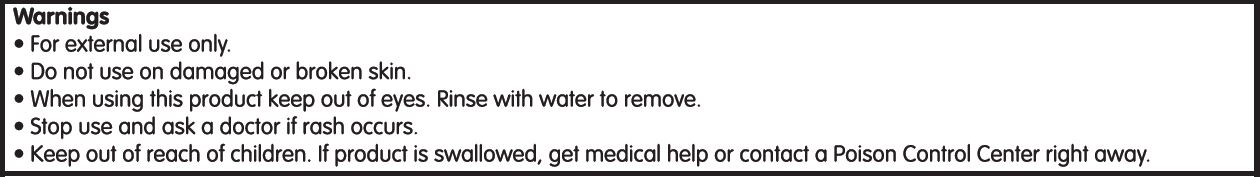 DRUG LABEL: Think Sport for Kids
NDC: 62932-266 | Form: STICK
Manufacturer: Private Label Select Ltd CO
Category: otc | Type: HUMAN OTC DRUG LABEL
Date: 20220104

ACTIVE INGREDIENTS: ZINC OXIDE 20 g/100 g
INACTIVE INGREDIENTS: CARNAUBA WAX; SHEA BUTTER; .ALPHA.-TOCOPHEROL, D-; COCONUT OIL; CANDELILLA WAX; SUNFLOWER OIL; WHITE WAX; .GAMMA.-TOCOPHEROL; CASTOR OIL; .BETA.-TOCOPHEROL; .DELTA.-TOCOPHEROL; ALOE VERA LEAF; COCOA BUTTER

Think Operations, Think Sport for Kids